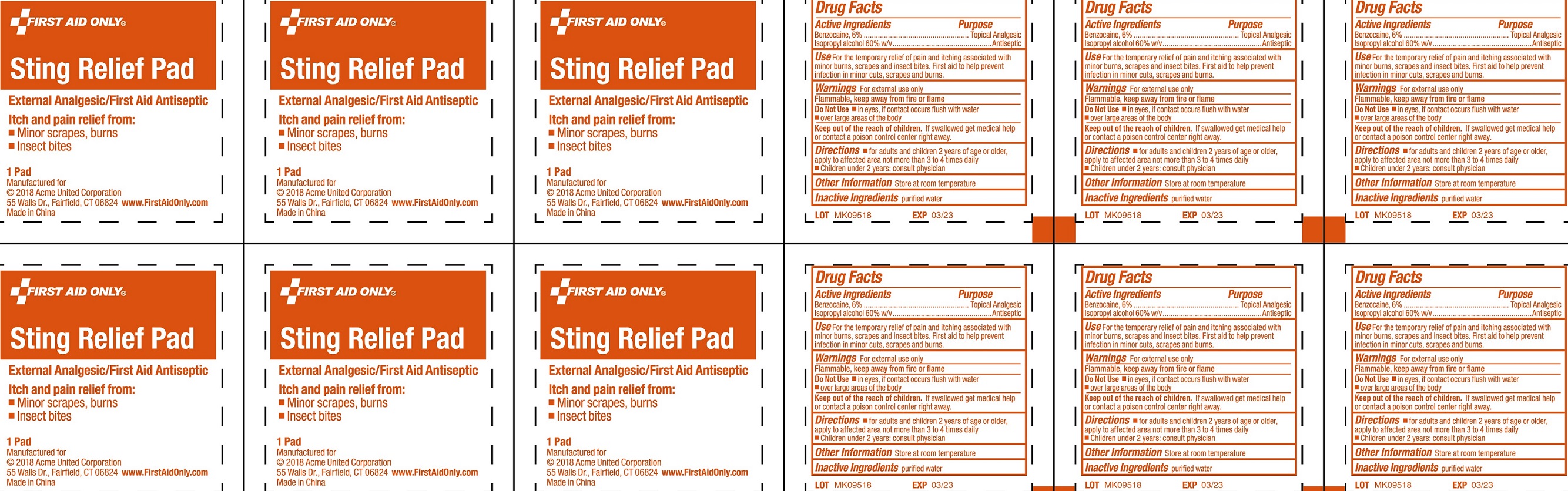 DRUG LABEL: Sting Relief Pad
NDC: 0924-5202 | Form: SWAB
Manufacturer: Acme United Corporation
Category: otc | Type: HUMAN OTC DRUG LABEL
Date: 20241119

ACTIVE INGREDIENTS: BENZOCAINE 60 mg/1 g; ISOPROPYL ALCOHOL 600 mg/1 g
INACTIVE INGREDIENTS: WATER

First Aid Only Sting Relief Pad

Active Ingredients

Benzocaine, 6%

Isopropyl alcohol 60% w/v

Purpose

Topical Analgesic

Antiseptic

Use

For the temporary relief of pain and itching associated with minor burns, scrapes and insect bites. First aid to help prevent infection in minor cuts, scrapes and burns.

Warnings

For external use only

Flammable, keep away from fire or flame

Do Not use

- in eyes, if contact occurs flush with water
- over large areas of the body

Keep out of the reach of children.

If swallowed get medical help or contact a poison control center right away.

Directions

- for adults and children 2 years of age or older, apply to affected area not more than 3 to 4 times daily
- Children under 2 years: consult ohysician

Other Information

Store at room temperature

Inactive Ingredients

purified water